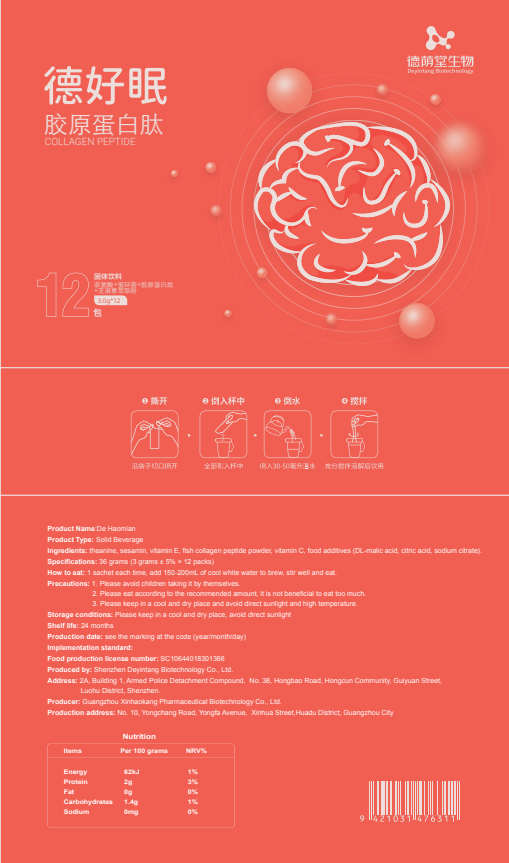 DRUG LABEL: De Haomian
NDC: 82570-014 | Form: POWDER
Manufacturer: Shenzhen Deyintang Biotechnology Co., Ltd.
Category: otc | Type: HUMAN OTC DRUG LABEL
Date: 20220221

ACTIVE INGREDIENTS: SESAMIN 7 g/100 g; ASCORBIC ACID 4 g/100 g; THEANINE 3 g/100 g; .ALPHA.-TOCOPHEROL 7 g/100 g; COLLAGEN, SOLUBLE, FISH SKIN 70 g/100 g
INACTIVE INGREDIENTS: MALIC ACID; SODIUM CITRATE; CITRIC ACID MONOHYDRATE

ACTIVE INGREDIENT

heanine,sesamin,vitaminE, fish collagen peptide powder, vitamin C

INACTIVE INGREDIENT

DL-malic acid, citric acid, sodium citrate

PURPOSE

health care

Please avoid children taking it by themselves.

How to eat

1 sachet each time, add 150-200mL of cool white water to brew, stir well and eat.

INDICATIONS AND USAGE

Please eat according to the recommended amount, it is not beneficial to eat too much.

Storage conditions

Please keep in a cool and dry place, avoid direct sunlight

WARNINGS

1.Please avoid children taking it by themselves.
2.Please eat according to the recommended amount, it is not beneficial to eat too much.

3.Please keep in a cool and dry place and avoid direct sunlight and high temperature.